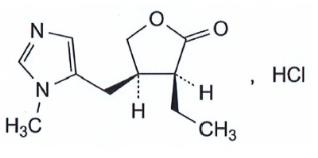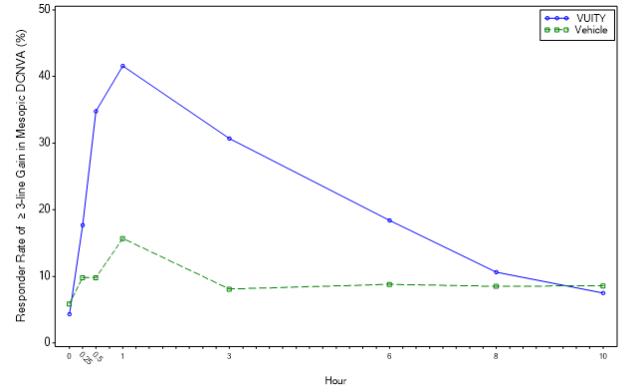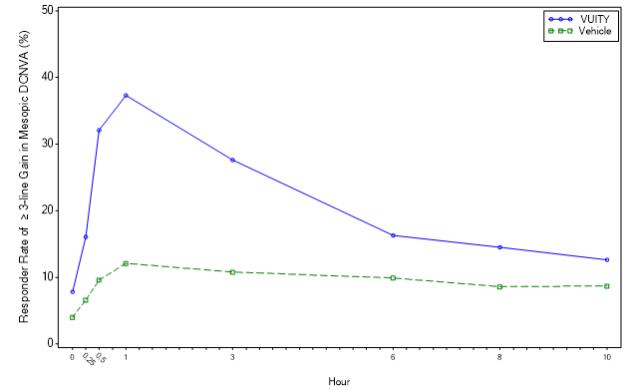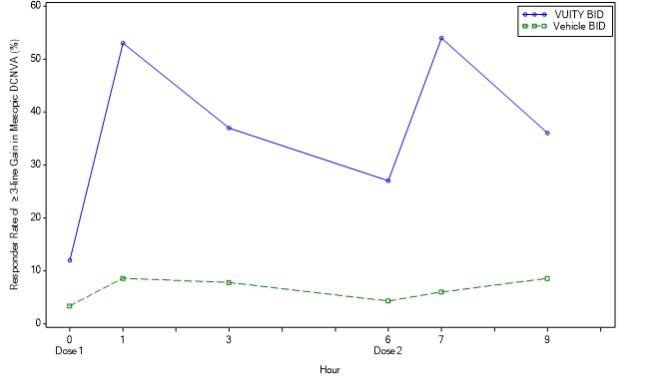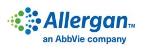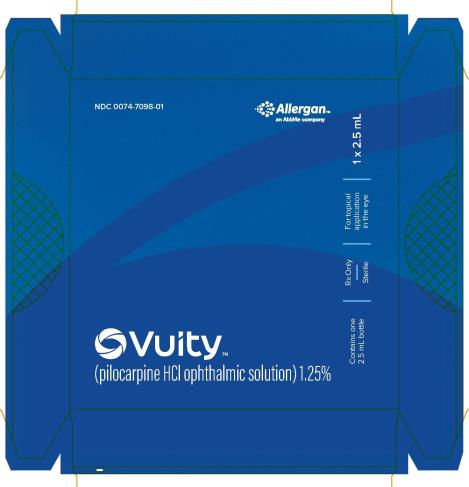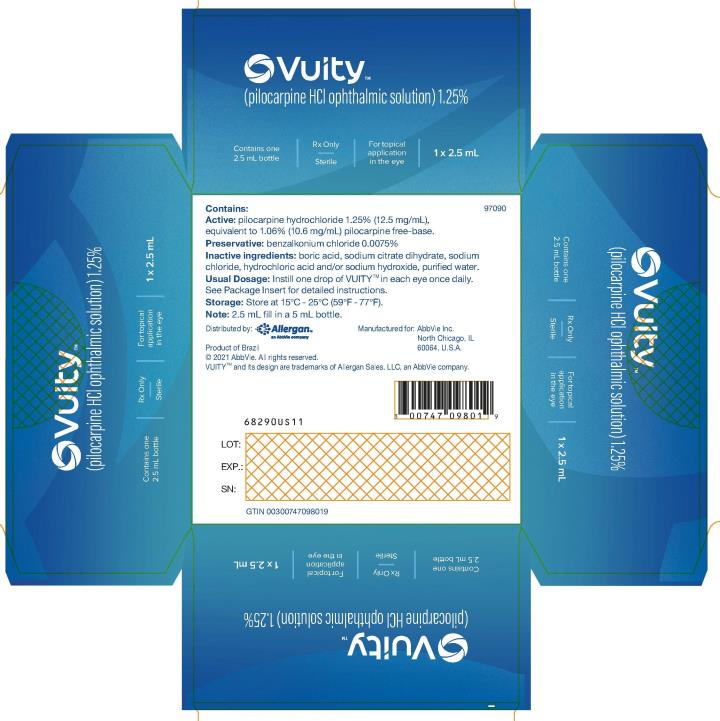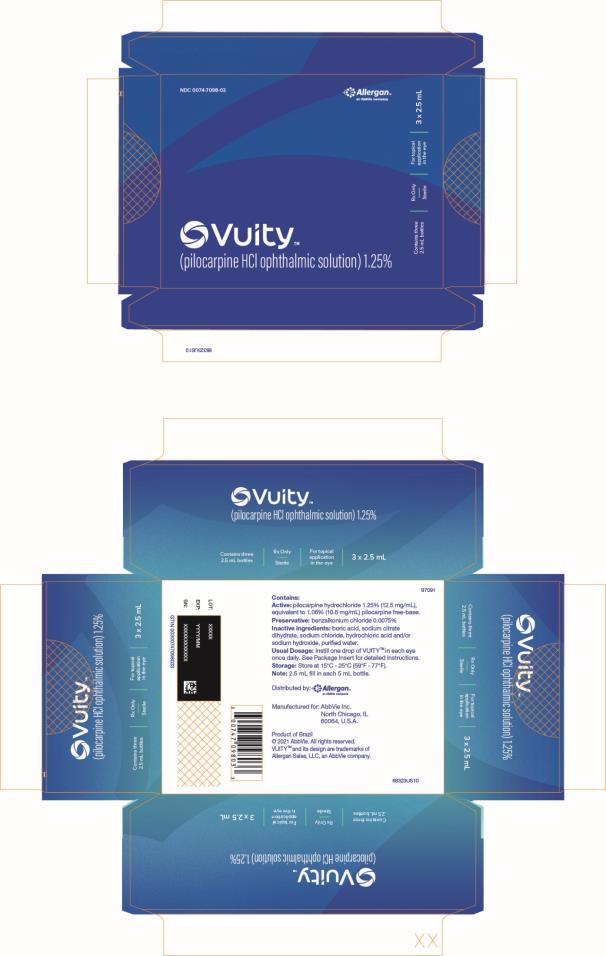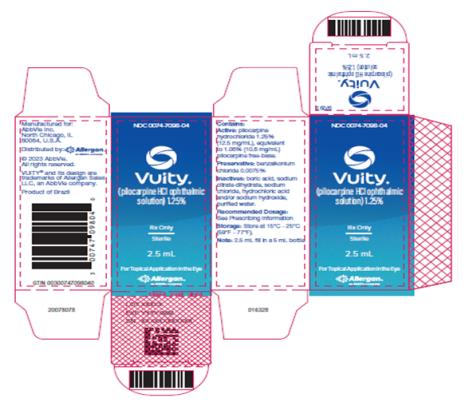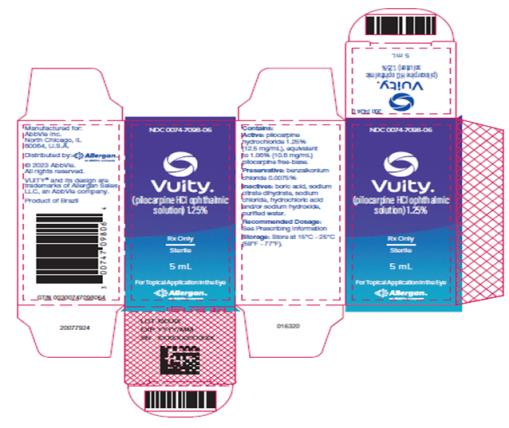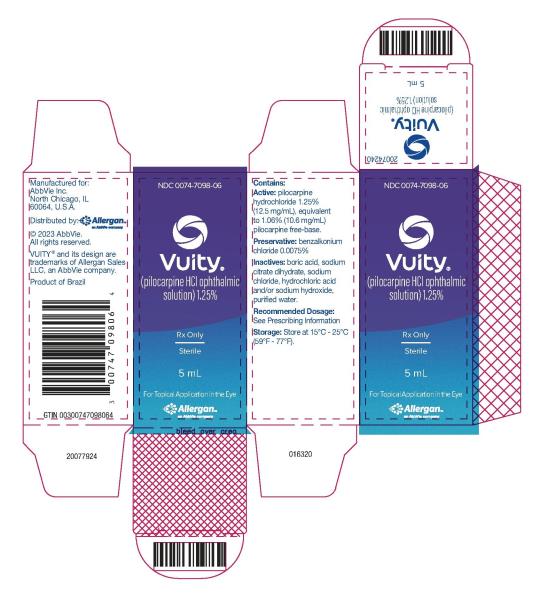 DRUG LABEL: VUITY
NDC: 0074-7098 | Form: SOLUTION/ DROPS
Manufacturer: AbbVie Inc.
Category: prescription | Type: HUMAN PRESCRIPTION DRUG LABEL
Date: 20230328

ACTIVE INGREDIENTS: Pilocarpine Hydrochloride 12.5 mg/1 mL
INACTIVE INGREDIENTS: BORIC ACID; TRISODIUM CITRATE DIHYDRATE; SODIUM CHLORIDE; WATER; HYDROCHLORIC ACID; SODIUM HYDROXIDE; BENZALKONIUM CHLORIDE

HIGHLIGHTS OF PRESCRIBING INFORMATION

These highlights do not include all the information needed to use VUITY safely and effectively. See full prescribing information for VUITY.
VUITY® (pilocarpine hydrochloride ophthalmic solution) 1.25%, for topical ophthalmic use
Initial U.S. Approval: 1974

RECENT MAJOR CHANGES

Warnings and Precautions, Blurred Vision (5.1) | 8/2022
Warnings and Precautions, Risk of Retinal Detachment (5.2) | 8/2022
Dosage and Administration (2) | 3/2023

1 INDICATIONS AND USAGE

VUITY is a cholinergic muscarinic receptor agonist indicated for the treatment of presbyopia in adults. (1)

2 DOSAGE AND ADMINISTRATION

Instill one drop of VUITY in each eye once daily. A second dose (one additional drop in each eye) may be administered 3-6 hours after the first dose. (2)

3 DOSAGE FORMS AND STRENGTHS

Ophthalmic solution containing pilocarpine hydrochloride 1.25%. (3)

4 CONTRAINDICATIONS

Hypersensitivity (4)

5 WARNINGS AND PRECAUTIONS

- Blurred Vision: Patients should be advised not to drive or operate machinery if vision is not clear (e.g., blurred vision). Exercise caution in night driving and other hazardous activities in poor illumination. (5.1)
- Risk of Retinal Detachment: Rare cases of retinal detachment and retinal tear have been reported with miotics, including VUITY. Individuals with pre-existing retinal disease are at increased risk. Therefore, examination of the retina is advised in all patients prior to initiation of therapy. Patients should be advised to seek immediate medical care with sudden onset of flashing lights, floaters, or vision loss. (5.2)
- Iritis: Caution is advised in patients with iritis. (5.3)

6 ADVERSE REACTIONS

Most common adverse reactions (>5%) are headache, conjunctival hyperemia, and eye irritation. (6.1)

To report SUSPECTED ADVERSE REACTIONS, contact Allergan at 1-800-678-1605 or FDA at 1-800-FDA-1088 or www.fda.gov/medwatch.

FULL PRESCRIBING INFORMATION

1 INDICATIONS AND USAGE

VUITY® is indicated for the treatment of presbyopia in adults.

2 DOSAGE AND ADMINISTRATION

The recommended dosage of VUITY is one drop in each eye once daily. A second dose (one additional drop in each eye) may be administered 3-6 hours after the first dose.

If more than one topical ophthalmic product is being used, the products should be administered at least 5 minutes apart.

3 DOSAGE FORMS AND STRENGTHS

VUITY (pilocarpine hydrochloride ophthalmic solution) is a clear, colorless, sterile ophthalmic solution containing 1.25% (12.5 mg/mL) of pilocarpine hydrochloride.

4 CONTRAINDICATIONS

VUITY is contraindicated in patients with known hypersensitivity to the active ingredient or to any of the excipients.

5 WARNINGS AND PRECAUTIONS

5.1 Blurred Vision

Miotics, including VUITY, may cause accommodative spasm. Patients should be advised not to drive or operate machinery if vision is not clear (e.g., blurred vision).

In addition, patients may experience temporary dim or dark vision with miotics, including VUITY. Patients should be advised to exercise caution in night driving and other hazardous activities in poor illumination.

5.2 Risk of Retinal Detachment

Rare cases of retinal detachment and retinal tear have been reported with miotics, including VUITY.

Individuals with pre-existing retinal disease are at increased risk. Therefore, examination of the retina is advised in all patients prior to the initiation of therapy.

Patients should be advised to seek immediate medical care with sudden onset of flashing lights, floaters, or vision loss.

5.3 Iritis

VUITY is not recommended to be used when iritis is present because adhesions (synechiae) may form between the iris and the lens.

5.4 Use with Contact Lenses

Contact lens wearers should be advised to remove their lenses prior to the instillation of VUITY and to wait 10 minutes after dosing before reinserting their contact lenses.

5.5 Potential for Eye Injury or Contamination

To prevent eye injury or contamination, care should be taken to avoid touching the dispensing bottle to the eye or to any other surface.

6 ADVERSE REACTIONS

The following clinically significant adverse reactions are described elsewhere in labeling:

- Hypersensitivity [see Contraindications (4)]

6.1 Clinical Trials Experience

Because clinical trials are conducted under widely varying conditions, adverse reaction rates observed in the clinical trials of a drug cannot be directly compared to rates in the clinical trials of another drug and may not reflect the rates observed in practice.

VUITY dosed once daily was evaluated in 375 participants with presbyopia in two randomized, double-masked, vehicle-controlled studies (GEMINI 1 and GEMINI 2) of 30 days duration. The most common adverse reactions reported in >5% of participants were headache and conjunctival hyperemia. Ocular adverse reactions reported in 1-5% of participants were blurred vision, eye pain, visual impairment, eye irritation, and increased lacrimation.

VUITY was also evaluated in 114 participants with presbyopia in a randomized, double-masked, vehicle-controlled 14-day study (VIRGO) in which participants received two doses of VUITY in each eye, 6 hours apart daily. The most common adverse reactions reported in >5 % of participants were headache and eye irritation. Ocular adverse reactions reported in 1-5% of participants were visual impairment, eye pain, blurred vision, and vitreous floaters.

6.2 Postmarketing Experience

The following adverse reactions have been identified during postapproval use of VUITY. Because these reactions are reported voluntarily from a population of uncertain size, it is not always possible to reliably estimate their frequency or establish a causal relationship to VUITY exposure.

Eye disorders: vitreous detachment, vitreomacular traction, retinal tear, retinal detachment.

8 USE IN SPECIFIC POPULATIONS

8.1 Pregnancy

Risk Summary
There are no adequate and well-controlled studies of VUITY administration in pregnant women to inform a drug-associated risk. Oral administration of pilocarpine to pregnant rats throughout organogenesis and lactation did not produce adverse effects at clinically relevant doses.

Data
Human Data
No adequate and well-controlled trials of VUITY have been conducted in pregnant women. In a retrospective case series of 15 women with glaucoma, 4 patients used ophthalmic pilocarpine either pre-pregnancy, during pregnancy or postpartum. There were no adverse effects observed in patients or in their infants.

Animal Data
In embryofetal development studies, oral administration of pilocarpine to pregnant rats throughout organogenesis produced maternal toxicity, skeletal anomalies and reduction in fetal body weight at 90 mg/kg/day (approximately 485-fold higher than the maximum human ophthalmic dose [MHOD] of 0.03 mg/kg/day assuming administration of 2 drops/eye/day, on a mg/m^2 basis).

In a peri-/postnatal study in rats, oral administration of pilocarpine during late gestation through lactation increased stillbirths at a dose of 36 mg/kg/day (approximately 195-fold higher than the MHOD). Decreased neonatal survival and reduced mean body weight of pups were observed at ≥18 mg/kg/day (approximately 100 times the maximum human ophthalmic dose of VUITY).

8.2 Lactation

Risk Summary
There is no information regarding the presence of pilocarpine in human milk, the effects on the breastfed infants, or the effects on milk production to inform risk of VUITY to an infant during lactation.

Pilocarpine and/or its metabolites are excreted in the milk of lactating rats. Systemic levels of pilocarpine following topical ocular administration are low [see Clinical Pharmacology (12.3)], and it is not known whether measurable levels of pilocarpine would be present in maternal milk following topical ocular administration.

The developmental and health benefits of breastfeeding should be considered along with the mother’s clinical need for VUITY and any potential adverse effects on the breastfed child from VUITY.

Data
Animal Data
Following a single oral administration of ^14C-pilocarpine to lactating rats, the radioactivity concentrations in milk were similar to those in plasma.

8.4 Pediatric Use

Presbyopia does not occur in the pediatric population.

8.5 Geriatric Use

Clinical studies of VUITY did not include participants aged 65 and over to determine whether they respond differently from younger participants. Other reported clinical experience with ophthalmic pilocarpine solutions have not identified overall differences in safety between elderly and younger participants.

10 OVERDOSAGE

Systemic toxicity following topical ocular administration of pilocarpine is rare, but occasionally patients who are sensitive may develop sweating and gastrointestinal overactivity. Accidental ingestion can produce sweating, salivation, nausea, tremors and slowing of the pulse and a decrease in blood pressure. In moderate overdosage, spontaneous recovery is to be expected and is aided by intravenous fluids to compensate for dehydration. For patients demonstrating severe poisoning, atropine, the pharmacologic antagonist to pilocarpine, should be used.

11 DESCRIPTION

VUITY (pilocarpine hydrochloride ophthalmic solution) 1.25% is a cholinergic muscarinic receptor agonist prepared as an isotonic, clear, colorless, sterile ophthalmic solution containing 1.25% of pilocarpine hydrochloride. The chemical name for pilocarpine hydrochloride is (3S,4R)-3-ethyl-4-[(1-methyl-1H-imidazol-5-yl)methyl]oxolan-2-one hydrochloride. Its molecular weight is 244.72 and its molecular formula is C11H16N2O2 · HCl. Its structural formula is:

Each mL of VUITY contains pilocarpine hydrochloride 1.25% (12.5 mg) as the active ingredient, equivalent to 1.06% (10.6 mg) pilocarpine free-base. Preservative is: benzalkonium chloride 0.0075%. Inactive ingredients in the ophthalmic solution are: boric acid, sodium citrate dihydrate, sodium chloride, purified water, and may also include hydrochloric acid and/or sodium hydroxide for pH adjustment to between 3.5 and 5.5, if necessary.

12 CLINICAL PHARMACOLOGY

12.1 Mechanism of Action

Pilocarpine hydrochloride is a cholinergic muscarinic agonist which activates muscarinic receptors located at smooth muscles such as the iris sphincter muscle and ciliary muscle. VUITY contracts the iris sphincter muscle, constricting the pupil to improve near and intermediate visual acuity while maintaining some pupillary response to light. VUITY also contracts the ciliary muscle and may shift the eye to a more myopic state.

12.3 Pharmacokinetics

Systemic exposure to pilocarpine was evaluated in 22 participants with presbyopia who were administered 1 drop of VUITY in each eye once daily for 30 days (GEMINI 1). The mean (SD) Cmax and AUC values from time 0 to last measurable concentration over 10-hour period post-last dose on Day 30 were 1.95 (0.98) ng/mL and 4.14 (2.16) ng·hr/mL, respectively. The median Tmax value on Day 30 was 0.3 hours postdose with a range from 0.2 to 0.5 hours postdose.

Systemic exposure to pilocarpine was also evaluated in 8 participants with presbyopia who were administered 1 drop of VUITY in each eye twice daily for 14 days (VIRGO). The Day 14 mean (SD) Cmax following first daily dosing was 1.81 (0.51) ng/mL and following second daily dosing was 2.12 (1.75) ng/mL. The Day 14 mean (SD) AUC over 6-hour post-dose following first daily dose was 4.35 (1.50) ng·hr/mL and following second daily dose was 4.22 (3.14) ng·hr/mL. There was no significant systemic drug accumulation over time, with accumulation index ratios between Day 1 and Day 14 based on AUC as 1.42 and 1.03 for the first and second daily dose, respectively.

13 NONCLINICAL TOXICOLOGY

13.1 Carcinogenesis, Mutagenesis, Impairment of Fertility

Carcinogenesis

Pilocarpine did not induce tumors in mice at any dosage level studied (up to 30 mg/kg/day; approximately 80-times the MHOD). In rats, an oral dose of 18 mg/kg/day (approximately 100 times the MHOD), resulted in a statistically significant increase in the incidence of benign pheochromocytomas in both male and female rats, and a statistically significant increase in the incidence of hepatocellular adenomas in female rats.

Mutagenesis

Pilocarpine did not show any potential to cause genetic toxicity in a series of studies that included: 1) bacterial assays (Salmonella and E. coli) for reverse gene mutations; 2) an in vitro chromosome aberration assay in a Chinese hamster ovary cell line; 3) an in vivo chromosome aberration assay (micronucleus test) in mice; and 4) a primary DNA damage assay (unscheduled DNA synthesis) in rat hepatocyte primary cultures.

Impairment of Fertility

Pilocarpine oral administration to male and female rats at a dosage of 18 mg/kg/day (100 times the MHOD) resulted in impaired reproductive function, including reduced fertility, decreased sperm motility, and morphologic evidence of abnormal sperm. It is unclear whether the reduction in fertility was due to effects on males, females, or both. In dogs, exposure to pilocarpine at a dosage of 3 mg/kg/day for 6 months resulted in evidence of impaired spermatogenesis (approximately 55 times the MHOD).

14 CLINICAL STUDIES

The efficacy of VUITY dosed once daily for the treatment of presbyopia was demonstrated in two 30‐Day Phase 3, randomized, double‐masked, vehicle‐controlled studies, namely GEMINI 1 (NCT03804268) and GEMINI 2 (NCT03857542). A total of 750 participants aged 40 to 55 years old with presbyopia were randomized (375 to VUITY group) in two studies and participants were instructed to administer one drop of VUITY or vehicle once daily in each eye.

In both studies, the proportion of participants gaining 3 lines or more in mesopic, high contrast, binocular distance corrected near visual acuity (DCNVA), without losing more than 1 line (5 letters) of corrected distance visual acuity (CDVA) with the same refractive correction was statistically significantly greater in the VUITY group compared to the vehicle group at Day 30, Hour 3 (see Table 1).

Table 1: Primary Efficacy Results from GEMINI 1 and GEMINI 2 Studies (Intent-to-Treat Population)
 | GEMINI 1 |  |  | GEMINI 2
 | VUITY N=163 | Vehicle N=160 | p-value | VUITY N=212 | Vehicle N=215 | p-value
Proportion of participants gaining 3-lines or more in mesopic DCNVA, without losing more than 1 line (5 letters) of CDVA at Day 30, Hour 3 | 31% | 8% | p<0.01 | 26% | 11% | p<0.01

Figures 1 and 2 present the proportion of participants who gained 3-lines or more in mesopic DCNVA at Day 30.

Figure 1: Proportion of Participants Achieving 3-Lines or More Improvement in Mesopic, High Contrast, Binocular DCNVA at Day 30 in GEMINI 1 (Intent-to-Treat Population)

Timepoint | Hour 0 | Hour 0.25 | Hour 0.5 | Hour 1 | Hour 3 | Hour 6 | Hour 8 | Hour 10
VUITY (%) | 4.3 | 17.7 | 34.8 | 41.6 | 30.7 | 18.4 | 10.6 | 7.5
Vehicle (%) | 5.9 | 9.8 | 9.8 | 15.7 | 8.1 | 8.8 | 8.5 | 8.6
Difference (95% CI) | -1.5 (-6.4, 3.3) | 7.9 (0.3, 15.5) | 25.0 (16.2, 33.8) | 25.9 (16.4, 35.5) | 22.5 (14.3, 30.8) | 9.7 (2.3, 17.0) | 2.1 (-4.4, 8.5) | -1.1 (-7.1, 5.0)

Figure 2: Proportion of Participants Achieving 3-lines or More Improvement in Mesopic, High Contrast, Binocular DCNVA at Day 30 in GEMINI 2 (Intent-to-Treat Population)

Timepoint | Hour 0 | Hour 0.25 | Hour 0.5 | Hour 1 | Hour 3 | Hour 6 | Hour 8 | Hour 10
VUITY (%) | 7.8 | 16.1 | 32.1 | 37.3 | 27.6 | 16.3 | 14.5 | 12.6
Vehicle (%) | 4.0 | 6.6 | 9.6 | 12.1 | 10.8 | 9.9 | 8.6 | 8.7
Difference (95% CI) | 3.8 (-0.9, 8.4) | 9.4 (3.2, 15.7) | 22.5 (14.7, 30.3) | 25.2 (17.0, 33.4) | 16.7 (9.1, 24.3) | 6.5 (-0.1, 13.1) | 5.9 (-0.5, 12.2) | 3.8 (-2.3, 10.0)

The efficacy of VUITY dosed twice daily for the treatment of presbyopia was also demonstrated in a 14-Day, randomized, double-masked, vehicle-controlled study, namely VIRGO (NCT04983589). A total of 230 participants aged 40 to 55 years old with presbyopia were randomized (114 to VUITY group) and participants were instructed to administer one drop of VUITY or vehicle twice daily in each eye, with each dose administered 6 hours apart.

In this study, the proportion of participants gaining 3 lines or more in mesopic, high contrast, binocular distance corrected near visual acuity (DCNVA), without losing more than 1 line (5 letters) of corrected distance visual acuity (CDVA) with the same refractive correction was statistically significantly greater in the VUITY group compared to the vehicle group at Day 14, Hour 9 (3 hours after the second dose) (see Table 2).

Table 2: Primary Efficacy Results from VIRGO (Intent-to-Treat Population)
 | VIRGO
 | VUITY BID N=114 | Vehicle BID N=116 | p-value
Proportion of participants gaining 3-lines or more in mesopic DCNVA, without losing more than 1 line (5 letters) of CDVA at Day 14, Hour 9 (3 hours after the second dose) | 35% | 8% | p< 0.01

Figure 3 presents the proportion of participants who gained 3-lines or more in mesopic DCNVA at Day 14.

Figure 3: Proportion of Participants Achieving 3-lines or More Improvement in Mesopic, High Contrast, Binocular DCNVA at Day 14 in VIRGO (Intent-to-Treat Population)

Timepoint | Hour 0 | Hour 1 | Hour 3 | Hour 6 | Hour 7 | Hour 9
VUITY BID (%) | 12.3 | 53.5 | 37.7 | 27.2 | 54.4 | 36.8
Vehicle BID (%) | 3.4 | 8.6 | 7.8 | 4.3 | 6.0 | 8.6
Difference (95% CI) | 8.8 (2.0, 15.7) | 44.9 (34.4, 55.4) | 30.0 (19.8, 40.1) | 22.9 (13.9, 31.8) | 48.4 (38.2, 58.5) | 28.2 (18.0, 38.4)

16 HOW SUPPLIED/STORAGE AND HANDLING

VUITY is supplied as an isotonic, clear, colorless sterile ophthalmic solution in colorless low density polyethylene (LDPE) ophthalmic dispenser bottles and tips, with dark green high impact polystyrene caps as follows:

2.5 mL fill in 5 mL bottle (Box containing 1 bottle) | NDC 0074-7098-01
2.5 mL fill in 5 mL bottle (Box containing 3 bottles) | NDC 0074-7098-03
2.5 mL fill in 5 mL bottle (Carton containing 1 bottle) | NDC 0074-7098-04
5 mL fill in 5 mL bottle (Carton) | NDC 0074-7098-06

Storage

Store at 15°C to 25°C (59°F to 77°F). After opening, VUITY can be used until the expiration date on the bottle.

17 PATIENT COUNSELING INFORMATION

Night Driving
VUITY may cause temporary dim or dark vision. Advise patients to exercise caution with night driving and when hazardous activities are undertaken in poor illumination [see Warnings and Precautions (5.1)].

Accommodative Spasm
Temporary problems when changing focus between near and distant objects may occur. Advise patients not to drive or use machinery if vision is not clear (e.g., blurred vision) [see Warnings and Precautions (5.1)].

When to Seek Physician Advice
Advise patients to seek immediate medical care with sudden onset of flashing lights, floaters, or vision loss [see Warnings and Precautions (5.2)].

Contact Lens Wear
Contact lens should be removed prior to the instillation of VUITY. Wait 10 minutes after dosing before reinserting contact lenses [see Warnings and Precautions (5.4)].

Avoiding Contamination of the Product
Do not touch dropper tip to any surface, as this may contaminate the contents [see Warnings and Precautions (5.5)].

Concomitant Topical Ocular Therapy
If more than one topical ophthalmic medication is being used, the medicines must be administered at least 5 minutes apart.

Distributed by: Allergan, an AbbVie company
Manufactured for:
AbbVie Inc.
North Chicago, IL 60064 USA

© 2023 AbbVie. All rights reserved.
VUITY and its design are trademarks of Allergan Sales, LLC, an AbbVie company.

v5.0USPI7098

PRINCIPAL DISPLAY PANEL

NDC 0074-7098-01

Vuity™

(pilocarpine HCI ophthalmic solution) 1.25%

Contains one
2.5 mL bottle

Rx Only

Sterile

For topical
application
in the eye

1 x 2.5 mL

Allergan™

An AbbVie company

PRINCIPAL DISPLAY PANEL

NDC 0074-7098-03

Vuity™

(pilocarpine HCI ophthalmic solution) 1.25%

Contains three
2.5 mL bottles

Rx Only

Sterile

For topical
application
in the eye

3 x 2.5 mL

Allergan™

An AbbVie company

PRINCIPAL DISPLAY PANEL

NDC 0074-7098-04

Vuity™

(pilocarpine HCI ophthalmic
solution) 1.25%

Rx Only

Sterile

2.5 mL

For Topical Application in the Eye

Allergan™

An AbbVie company

PRINCIPAL DISPLAY PANEL

NDC 0074-7098-05

Professional Sample
Not for Resale

Vuity™

(pilocarpine HCI ophthalmic
solution) 1.25%

Rx Only

Sterile

1.5 mL

For Topical Application in the Eye

Allergan™

An AbbVie company

PRINCIPAL DISPLAY PANEL

NDC: 0074-7098-06

Vuity®

(pilocarpine HCI ophthalmic
solution) 1.25%

Rx Only

Sterile

5 mL

For Topical Application in the Eye

Allergan™

An AbbVie company